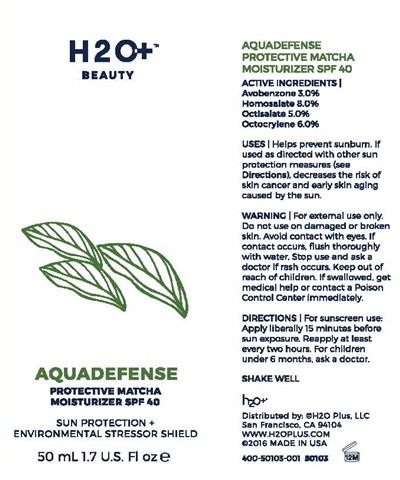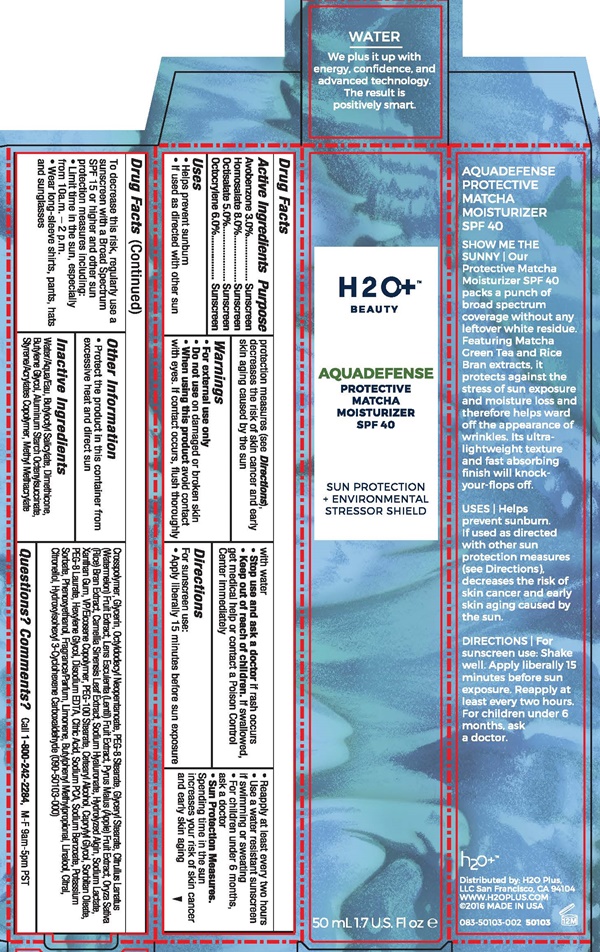 DRUG LABEL: H2O Beauty AQUADEFENSE
NDC: 54111-132 | Form: LOTION
Manufacturer: Bentley Laboratories, LLC
Category: otc | Type: HUMAN OTC DRUG LABEL
Date: 20181219

ACTIVE INGREDIENTS: AVOBENZONE 1.5 g/50 mL; HOMOSALATE 4 g/50 mL; OCTISALATE 2.5 g/50 mL; OCTOCRYLENE 3 g/50 mL
INACTIVE INGREDIENTS: WATER; BUTYLOCTYL SALICYLATE; DIMETHICONE; BUTYLENE GLYCOL; ALUMINUM STARCH OCTENYLSUCCINATE; STYRENE/ACRYLAMIDE COPOLYMER (MW 500000); METHYL METHACRYLATE/GLYCOL DIMETHACRYLATE CROSSPOLYMER; GLYCERIN; OCTYLDODECYL NEOPENTANOATE; PEG-8 STEARATE; GLYCERYL STEARATE CITRATE; WATERMELON; LENS CULINARIS FRUIT; APPLE; RICE BRAN; GREEN TEA LEAF; HYALURONATE SODIUM; SODIUM ALGINATE; SODIUM LACTATE; XANTHAN GUM; VINYLPYRROLIDONE/EICOSENE COPOLYMER; PEG-100 STEARATE; CETOSTEARYL ALCOHOL; CAPRYLYL GLYCOL; SORBITAN MONOOLEATE; PEG-8 LAURATE; HEXYLENE GLYCOL; EDETATE DISODIUM ANHYDROUS; CITRIC ACID MONOHYDRATE; SODIUM PYRROLIDONE CARBOXYLATE; SODIUM BENZOATE; POTASSIUM SORBATE; PHENOXYETHANOL; LIMONENE, (+)-; BUTYLPHENYL METHYLPROPIONAL; LINALOOL, (+/-)-; CITRAL; .BETA.-CITRONELLOL, (R)-; HYDROXYISOHEXYL 3-CYCLOHEXENE CARBOXALDEHYDE

H2O+ Beauty AQUADEFENSE PROTECTIVE MATCHA MOISTURIZER SPF 40 - 132

Drug Facts Active Ingredients

Avobenzone 3.0%
Homosalate 8.0%
Octisalate 5.0%
Octocrylene 6.0%

Purpose

Sunscreen

Uses

- Helps prevent sunburn
- If used as directed with other sun protection measures (see Directions), decreases the risk of skin cancer and early skin aging caused by the sun

Warnings

- For external use only
- Do not use on damaged or broken skin
- When using this product avoid contact with eyes. If contact occurs, flush thoroughly with water
- Stop use and ask a doctor if rash occurs

Keep out of reach of children.

If swallowed, get medical help or contact a Poison Control Center immediately.

Directions

For sunscreen use:

- Apply liberally 15 minutes before sun exposure
- Reapply at least every two hours
- Use a water resistant sunscreen if swimming or sweating
- For children under 6 months, ask a doctor
- Sun Protection Measures.

Spending time in the sun increases your risk of skin cancer and early skin aging. To decrease this risk, regularly use a sunscreen with a Broad Spectrum SPF 15 or higher and other sun protection measures including:

- Limit time in the sun, especially from 10a.m. - 2p.m.
- Wear long-sleeve shirts, pants, hats and sunglasses.

Other Information

- Protect the product in this container from excessive heat and direct sun

Inactive Ingredients

Water/Aqua/Eau, Butyloctyl Salicylate, Dimethicone, Butylene Glycol, Aluminum Starch Octenylsuccinate, Styrene/Acrylates Copolymer, Methyl Methacrylate Crosspolymer, Glycerin, Octyldodecyl Neopentanoate, PEG-8 Stearate, Glyceryl Stearate, Citrullus Lanatus (Watermelon) Fruit Extract, Lens Esculanta (Lentil) Fruit Extract, Pyrus Malus (Apple) Fruit Extract, Oryza Sativa (Rice) Bran Extract, Camellia Sinensis Leaf Extract, Sodium Hyaluronate, Hydrolyzed Algin, Sodium Lactate, Xanthan Gum, VP/Eicosene Copolymer, PEG-100 stearate, Cetearyl Alcohol, Caprylyl Glycol, Sorbitan Oleate, PEG-8 Laurate, Hexylene Glycol, Disodium EDTA, Citric Acid, Sodium PCA, Sodium Benzoate, Potassium Sorbate, Phenowyethanol, Fragrance/Parfum, Limonene, Buthyphenyl Methylpropional, Linalool, Citral, Citronellol, Hydroxyisohexyl 3-Cyclohexene Carboxaldehyde (090-50103-000)

Questions ? Comments ?

Call 1-800-242-2284, M-F 9am - 5pm PST

H2O+™ BEAUTY AQUADEFENSE PROTECTIVE MATCHA MOISTURIZER SPF 40 product label

H2O+™ BEAUTY AQUADEFENSE
PROTECTIVE MATCHA MOISTURIZER SPF 40

SUN PROTECTION + ENVIROMENTAL
STRESSOR SHIELD

50 mL 1.7 U.S. FL oz

AQUADEFENSE PROTECTIVE MATCHA MOISTURIZER SPF 40

SHOW ME THE SUN l Our Protective Matcha Moisturizer SPF 40 packs a punch of broad spectrum coverage without any leftover white residue. Featuring Matcha Green Tea and Rice Bran extracts, it protects against the stress of sun exposure and moisture loss and therefore helps ward off the appearance of wrinkles. Its ultra-lightweight texture and fast absorbing finish will knock-your-flops off.

USES l Helps prevent sunburn. If used as directed with other sun measures (see Directions), decreases the risk of skin cancer and early skin aging caused by the sun.

DIRECTIONS l For sunscreen use: Shake well. Apply liberally 15 minutes before sun exposure. Reapply at least every two hours. For children under 6 months, ask a doctor.

H2O+™

Distributed by: H2o Plus, LLC

San Francisco, CA. 94104
www.H2OPLUS.COM

©2016 MADE IN USA

083-50103-002 50103